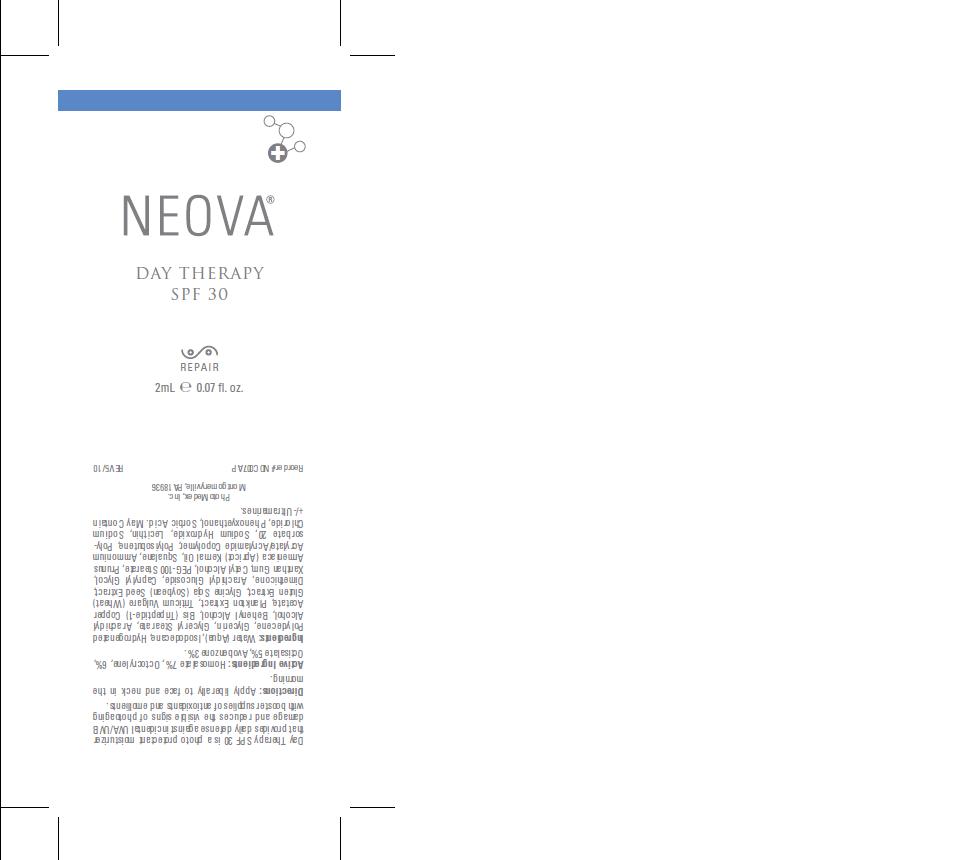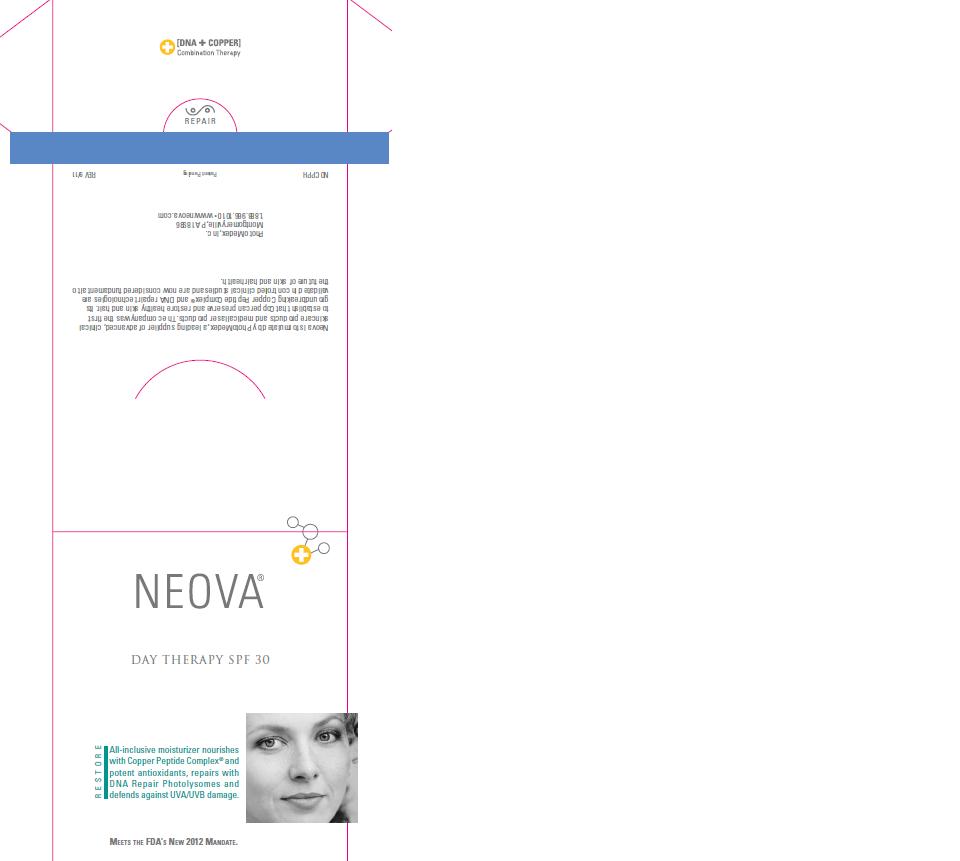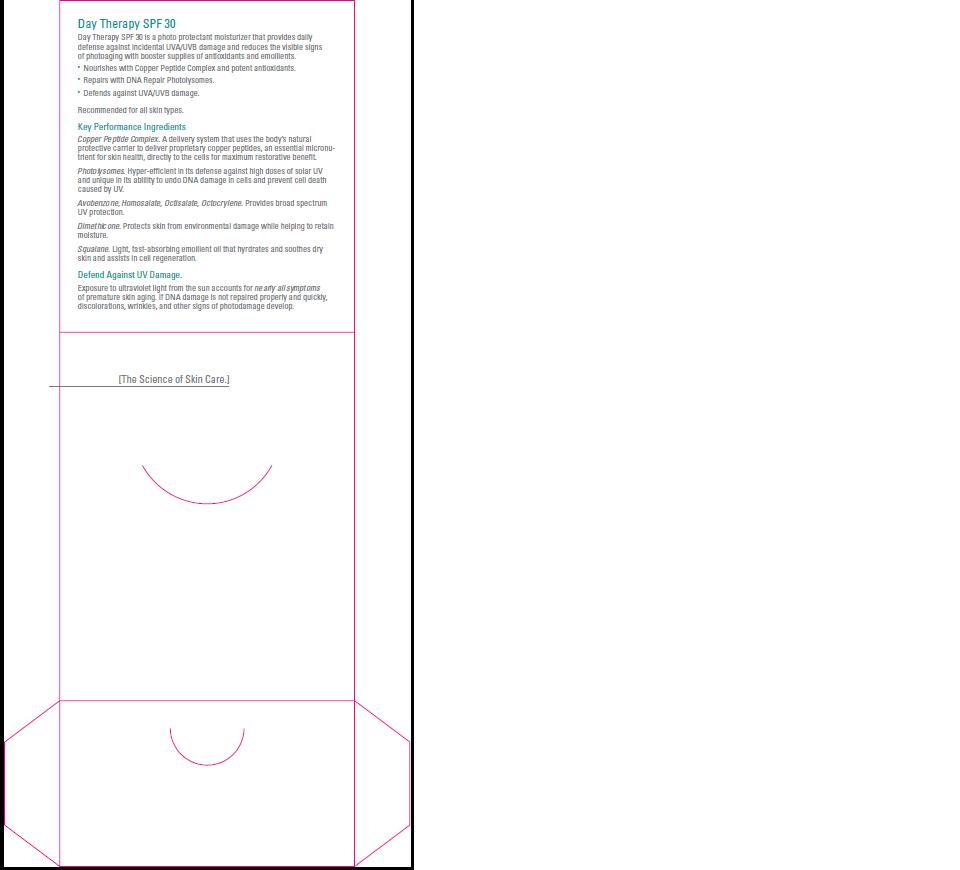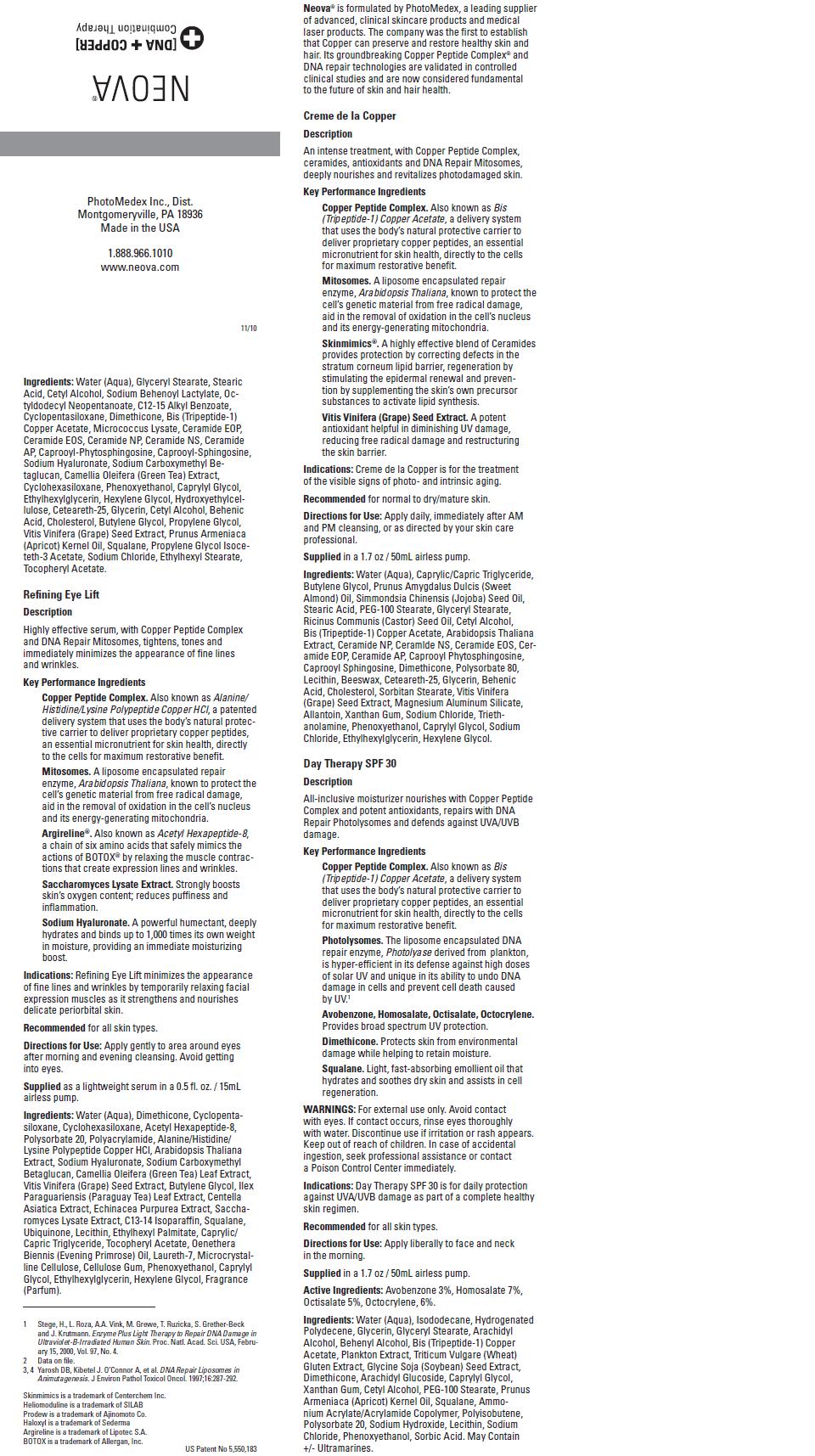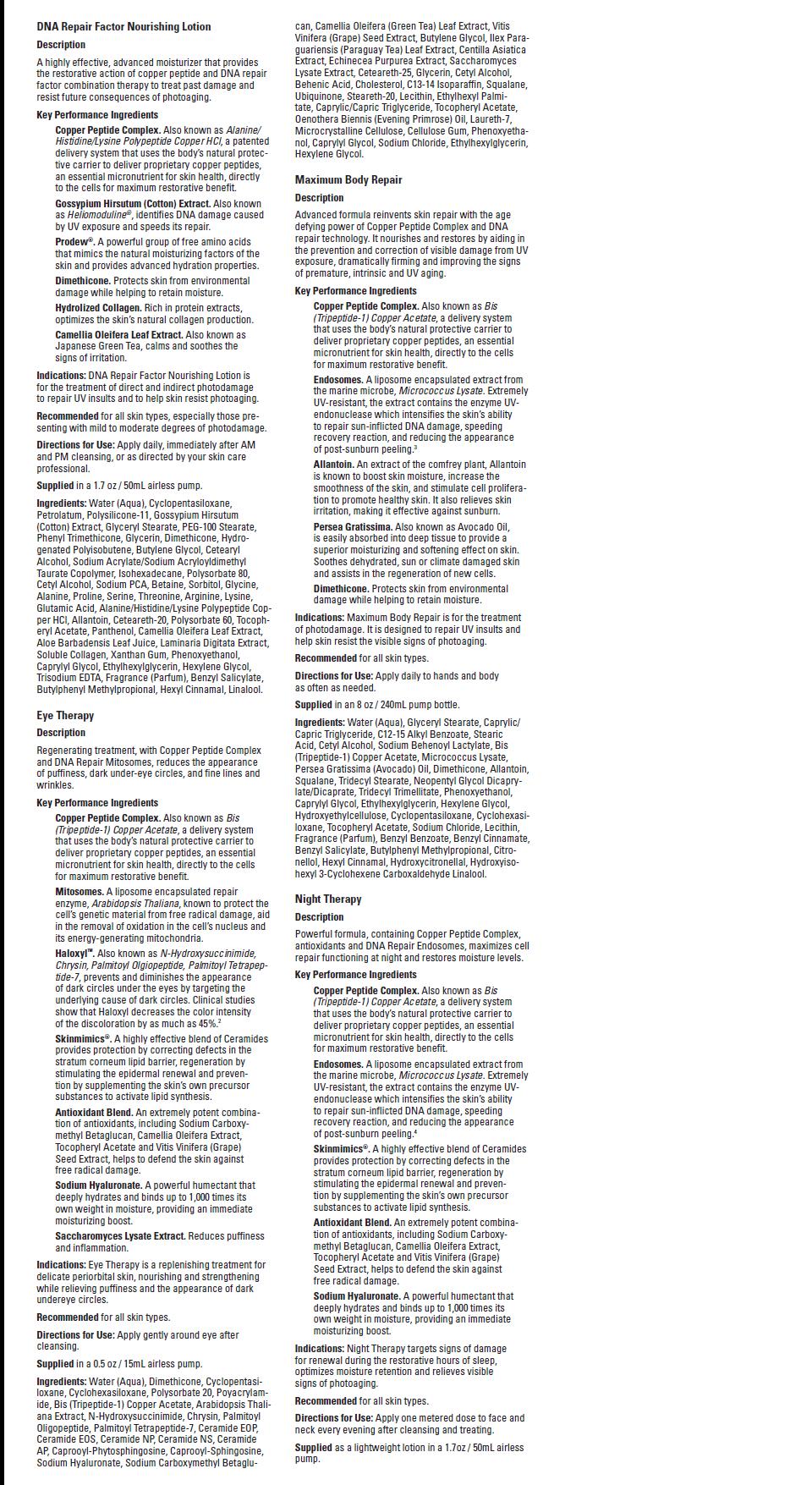 DRUG LABEL: Neova Day Therapy
NDC: 62362-184 | Form: LOTION
Manufacturer: PhotoMedex, Inc.
Category: otc | Type: HUMAN OTC DRUG LABEL
Date: 20120111

ACTIVE INGREDIENTS: Homosalate 7 mL/100 mL; Octocrylene 6 mL/100 mL; Octisalate 5 mL/100 mL; Avobenzone 3 mL/100 mL
INACTIVE INGREDIENTS: Water; Isododecane; Hydrogenated Polydecene (550 MW); Glycerin; Glyceryl Monostearate; Arachidyl Alcohol; Docosanol; Prezatide Copper Acetate; Soybean; Dimethicone; Arachidyl Glucoside; Caprylyl Glycol; Xanthan Gum; Cetyl Alcohol; PEG-100 Stearate; Apricot Kernel Oil; Squalane; Polyisobutylene (1300 MW); Polysorbate 20; Sodium Hydroxide; Lecithin, Soybean; Sodium Chloride; Phenoxyethanol; Sorbic Acid

Neova Day Therapy - SPF 30 - 2ML - 0.07 FL. OZ - package insert

WARNINGS:

For external use only. Avoid contact
with eyes. If contact occurs, rinse eyes thoroughly
with water. Discontinue use if irritation or rash appears.
Keep out of reach of children. In case of accidental
ingestion, seek professional assistance or contact
a Poison Control Center immediately.

Directions:

Apply liberally to face and neck in the morning.

Supplied

in a 1.7 oz / 50mL airless pump.

Active Ingredients:

Homosalate 7%, Octocrylene, 6%,
Octisalate 5%, Avobenzone 3%

Purpose:

Sunscreen

Ingredients:

Water (Aqua), Isododecane, Hydrogenated
Polydecene, Glycerin, Glyceryl Stearate, Arachidyl
Alcohol, Behenyl Alcohol, Bis (Tripeptide-1) Copper
Acetate, Plankton Extract, Triticum Vulgare (Wheat)
Gluten Extract, Glycine Soja (Soybean) Seed Extract,
Dimethicone, Arachidyl Glucoside, Caprylyl Glycol,
Xanthan Gum, Cetyl Alcohol, PEG-100 Stearate, Prunus
Armeniaca (Apricot) Kernal Oil, Squalane, Ammonium
Acrylate/Acrylamide Copolymer, Polyisobutene, Polysorbate
20, Sodium Hydroxide, Lecithin, Sodium
Chloride, Phenoxyethanol, Sorbic Acid. May Contain
+/- Ultramarines.

Image of Packet, Packet Holder, Package Insert

DayTherapyFoilPacket.jpg PacketHolderDayTherapypg1.jpg PacketHolderDayTherapypg2.jpg PkgInsertComboTherapypg1.jpg PkgInsertComboTherapypg2.jpg